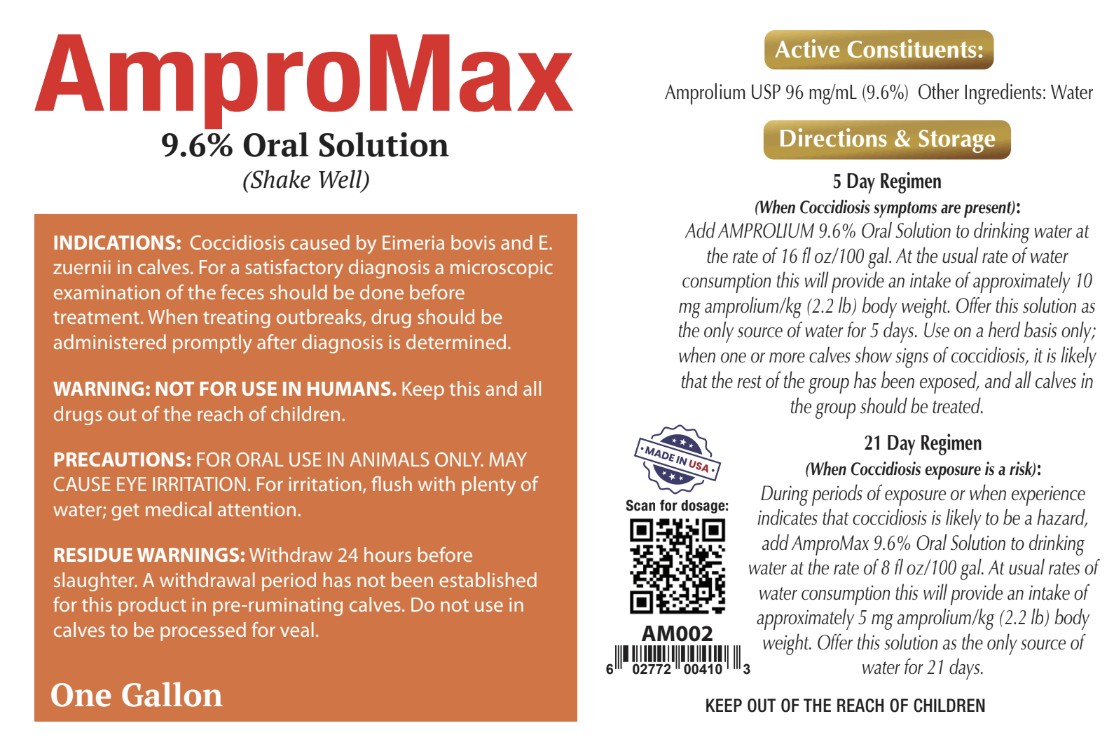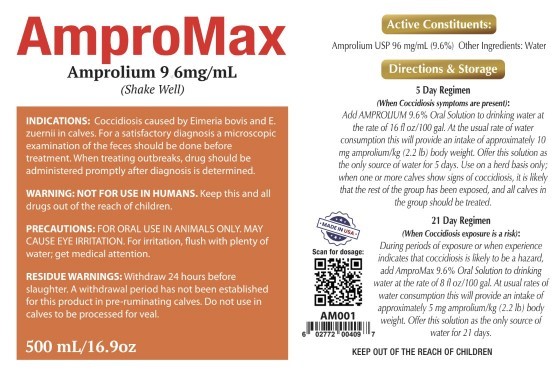 DRUG LABEL: Ampromax
NDC: 86213-772 | Form: SOLUTION
Manufacturer: Vetr LLC
Category: animal | Type: OTC ANIMAL DRUG LABEL
Date: 20250610

ACTIVE INGREDIENTS: AMPROLIUM 96 mg/1 mL
INACTIVE INGREDIENTS: WATER

Vetr Ampromax (amprolium, 9.6% oral solution)

WARNINGS AND PRECAUTIONS

WARNING: NOT FOR USE IN HUMANS. Keep this and all drugs out of the reach of children. FOR ORAL USE IN ANIMALS ONLY. MAY CAUSE EYE IRRITATION. For irritation, flush with water and seek medical attention. RESUDUE WARNING: Withdraw 24 h before slaughter. A withdrawl period has not been established for this product in pre-ruminating calves. Do not use in calves to be processed for veal.

Shake well before use.

5 Day Regimen (coccidiosis symptoms present): Add Ampromax (9.6% amprolium) oral solution to drinking water at the rate of 16 fl oz/100 gal (473 mL/378.5 mL). At the usual rate of water consumption, this will provide intake of approximately 10 mg amprolium/kg body weight (2.2 lbs). Offer this solution as the only source of water for 5 days. Use on a herd basis only; when one or more calves show signs of coccidiosis, it is likely that the rest of the group has been exposed and all calves should be treated.

21 Day Regimen(coccidiosis exposure risk): During periods of exposure, or when experience indicates environmental coccidiosis risk, add Ampromax (9.6% amprolium) oral solution to drinking water at the rate of 8 fl oz/100 gal (237 mL/378.5 mL). At usual rates of consumption, this will provide approximately 5 mg amprolium/kg body weight (2.2 lbs). Offer this solution as the only source of water for 21 days.

STORAGE AND HANDLING

Store at room temperature, at or below 25 C (<77 F)

ACTIVE INGREDIENT

Amprolium USP, 96 mg/mL (9.6% w/v)

INACTIVE INGREDIENT

Purified water, preservative.